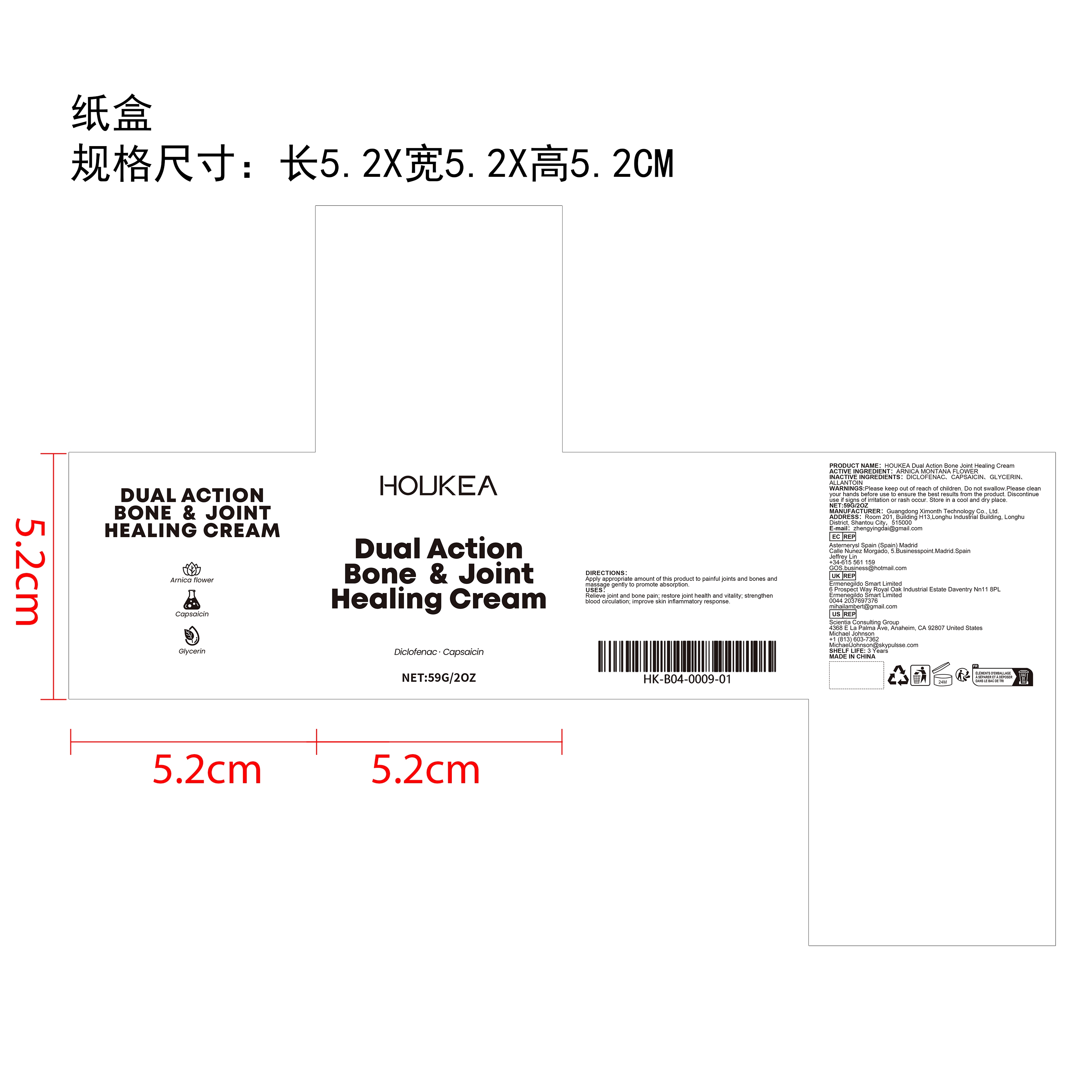 DRUG LABEL: HOUKEA Dual Action Bone Joint Healing Cream
NDC: 84660-087 | Form: CREAM
Manufacturer: Guangdong Ximonth Technology Co., Ltd.
Category: otc | Type: HUMAN OTC DRUG LABEL
Date: 20241028

ACTIVE INGREDIENTS: ARNICA MONTANA FLOWER 17.7 g/59 g
INACTIVE INGREDIENTS: CAPSAICIN 8.85 g/59 g; ALLANTOIN 17.7 g/59 g; GLYCERIN 8.85 g/59 g; DICLOFENAC 5.9 g/59 g

ACTIVE INGREDIENT

ARNICA MONTANA FLOWER

PURPOSE

Relieve joint and bone pain; restore joint health and vitality; strengthen blood circulation; improve skin inflammatory response.

USES

Apply appropriate amount of this product to painful joints and bones and massage gently to promote absorption.

WARNINGS

Please keep out of reach of children. Do not swallow.Please clean your hands before use to ensure the best results from the product. Discontinue use if signs of irritation or rash occur. Store in a cool and dry place.

STOP USE

Discontinue use if signs of irritation or rash occur.

DO NOT USE

Discontinue use if signs of irritation or rash occur.

KEEP OUT OF REACH OF CHILDREN

Please keep out of reach of children. Do not swallow.

STORAGE AND HANDLING

Store in a cool and dry place.

INACTIVE INGREDIENT

DICLOFENAC、CAPSAICIN、GLYCERIN、ALLANTOIN